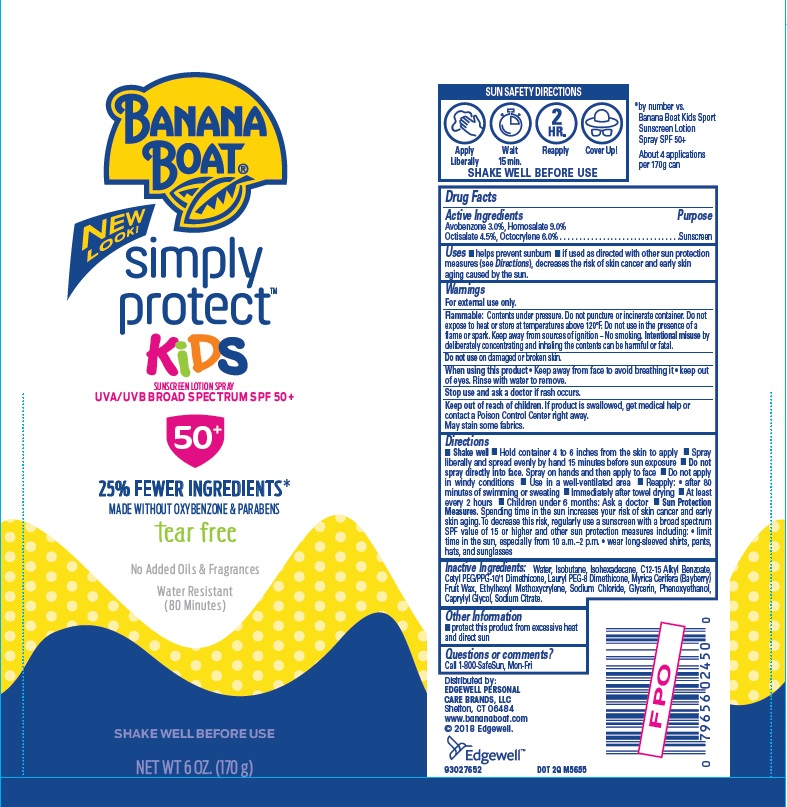 DRUG LABEL: Banana Boat
NDC: 63354-039 | Form: SPRAY
Manufacturer: Edgewell Personal Care Brands, LLC
Category: otc | Type: HUMAN OTC DRUG LABEL
Date: 20251106

ACTIVE INGREDIENTS: OCTISALATE 4.5 g/100 g; OCTOCRYLENE 6 g/100 g; AVOBENZONE 3 g/100 g; HOMOSALATE 9 g/100 g
INACTIVE INGREDIENTS: MORELLA CERIFERA FRUIT WAX; PHENOXYETHANOL; SODIUM CITRATE; WATER; ISOBUTANE; ETHYLHEXYL METHOXYCRYLENE; ISOHEXADECANE; ALKYL (C12-15) BENZOATE; CETYL PEG/PPG-10/1 DIMETHICONE (HLB 2); SODIUM CHLORIDE; GLYCERIN; CAPRYLYL GLYCOL

Active Ingredient

Avobenzone 3%, Homosalate 9%, Octisalate 4.5%, Octocrylene 6%

Purpose

Sunscreen

Uses

Helps prevent sunburn

If used as directed with other sun protection measures (see Directions), decreases the risk of skin cancer and early skin aging caused by the sun.

Warnings

For external use only.

Flammable

Contents under pressure. Do not puncture or incinerate container. Do not expose to heat or store at temperatures above 120°F. Do not use in the presence of a flame or spark. Keep away from sources of ignition – No smoking. Intentional misuse by deliberately concentrating and inhaling the contents can be harmful or fatal.

Do not use

on damaged or broken skin.

When using this product

Keep away from face to avoid breathing it. Keep out of eyes. Rinse with water to remove.

Stop use and ask a doctor

if rash occurs.

Keep out of reach of children

If product is swallowed, get medical help or contact a Poison Control Center right away.

May stain

some fabrics.

Directions

Shake well. Hold container 4 to 6 inches from the skin to apply. Spray liberally and spread evenly by hand 15 minutes before sun exposure. Do not spray directly into face. Spray on hands and then apply to face. Do not apply in windy conditions. Use in a well-ventilated area. Reapply: • after 80 minutes of swimming or sweating. Immediately after towel drying. At least every 2 hours. Children under 6 months: Ask a doctor. Sun Protection Measures. Spending time in the sun increases your risk of skin cancer and early
skin aging. To decrease this risk, regularly use a sunscreen with a broad spectrum SPF value of 15 or higher and other sun protection measures including: • limit time in the sun, especially from 10 a.m.–2 p.m. • wear long-sleeved shirts, pants, hats, and sunglasses

Inactive Ingredients

Water, Isobutane, Isohexadecane, C12-15 Alkyl Benzoate, Cetyl PEG/PPG-10/1 Dimethicone, Lauryl PEG-8 Dimethicone, Myrica Cerifera (Bayberry) Fruit Wax, Ethylhexyl Methoxycrylene, Sodium Chloride, Glycerin, Phenoxyethanol, Caprylyl Glycol, Sodium Citrate.

Other Information

protect this product from excessive heat and direct sun

Questions or comments?

Call 1-800-SafeSun, Mon-Fri

PACKAGE LABEL

BANANA

BOAT

Simply

Protect

KIDS

SUNSCREEN LOTION SPRAY

UVA/UVB BROAD SPECTRUM SPF 50+

50+

25% FEWER INGREDIENTS

MADE WITHOUT OXYBENZONE & PARABENS

tear free

No Added Oils & Fragrances

Water Resistant

(80 Minutes)

SHAKE WELL BEFORE USE